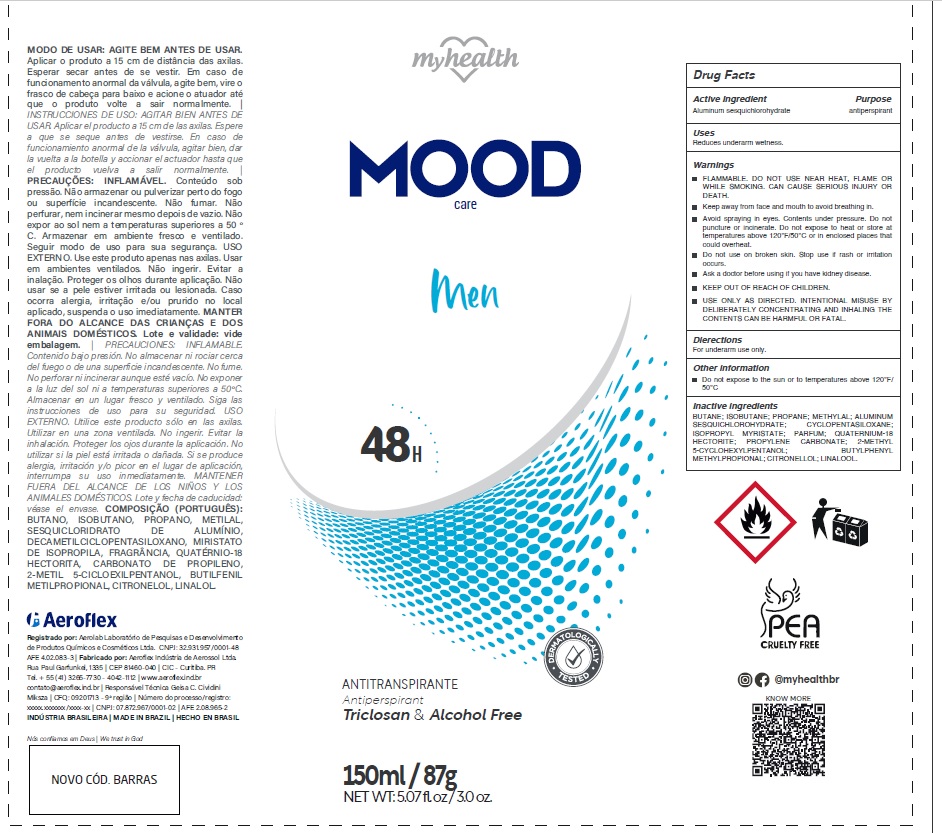 DRUG LABEL: MyHealth Mood Care Men
NDC: 80661-009 | Form: AEROSOL, SPRAY
Manufacturer: Aeroflex Industria de Aerosol Ltda
Category: otc | Type: HUMAN OTC DRUG LABEL
Date: 20251031

ACTIVE INGREDIENTS: ALUMINUM SESQUICHLOROHYDRATE 25 g/100 mL
INACTIVE INGREDIENTS: BUTANE; ISOBUTANE; PROPANE; METHYLAL; CYCLOMETHICONE 5; ISOPROPYL MYRISTATE; QUATERNIUM-18; HECTORITE; PROPYLENE CARBONATE; 2-METHYL 5-CYCLOHEXYLPENTANOL; BUTYLPHENYL METHYLPROPIONAL; .BETA.-CITRONELLOL, (R)-; LINALOOL, (+/-)-

Active Ingredients

Aluminum sesquichlorohydrate 25%

Purpose

Antiperspirant

Uses

Reduces underarm wetness.

Warnings

- FLAMMABLE. DO NOT USE NEAR HEAT, FLAME OR WHILE SMOKING. CAN CAUSE SERIOUS INJURY OR DEATH.
- Keep away from face and mouth to avoid breathing in.
- Avoid spraying in eyes. Contents under pressure. Do not puncture or incinerate. Do not expose to heat or store at temperatures above 120°F/50°C or in enclosed places that could overheat.
- Do not use on broken skin. Stop use if rash or irritation occurs.
- Ask a doctor before using if you have kidney disease.
- KEEP OUT OF REACH OF CHILDREN.
- USE ONLY AS DIRECTED. INTENTIONAL MISUSE BY DELIBERATELY CONCENTRATING AND INHALING THE CONTENTS CAN BE HARMFUL OR FATAL.

Directions

For underarm use only.

Other Information

Do not expose to the sun or to temperatures above 120°F/ 50°C

Inactive Ingredients

butane, isobutane, propane, methylal, cyclopentasiloxane, isopropyl myristate, parfum, quaternium-18, hectorite, propylene carbonate, 2-methyl 5-cyclohexylpentanol,butylphenyl methylpropional, citronellol, linalool